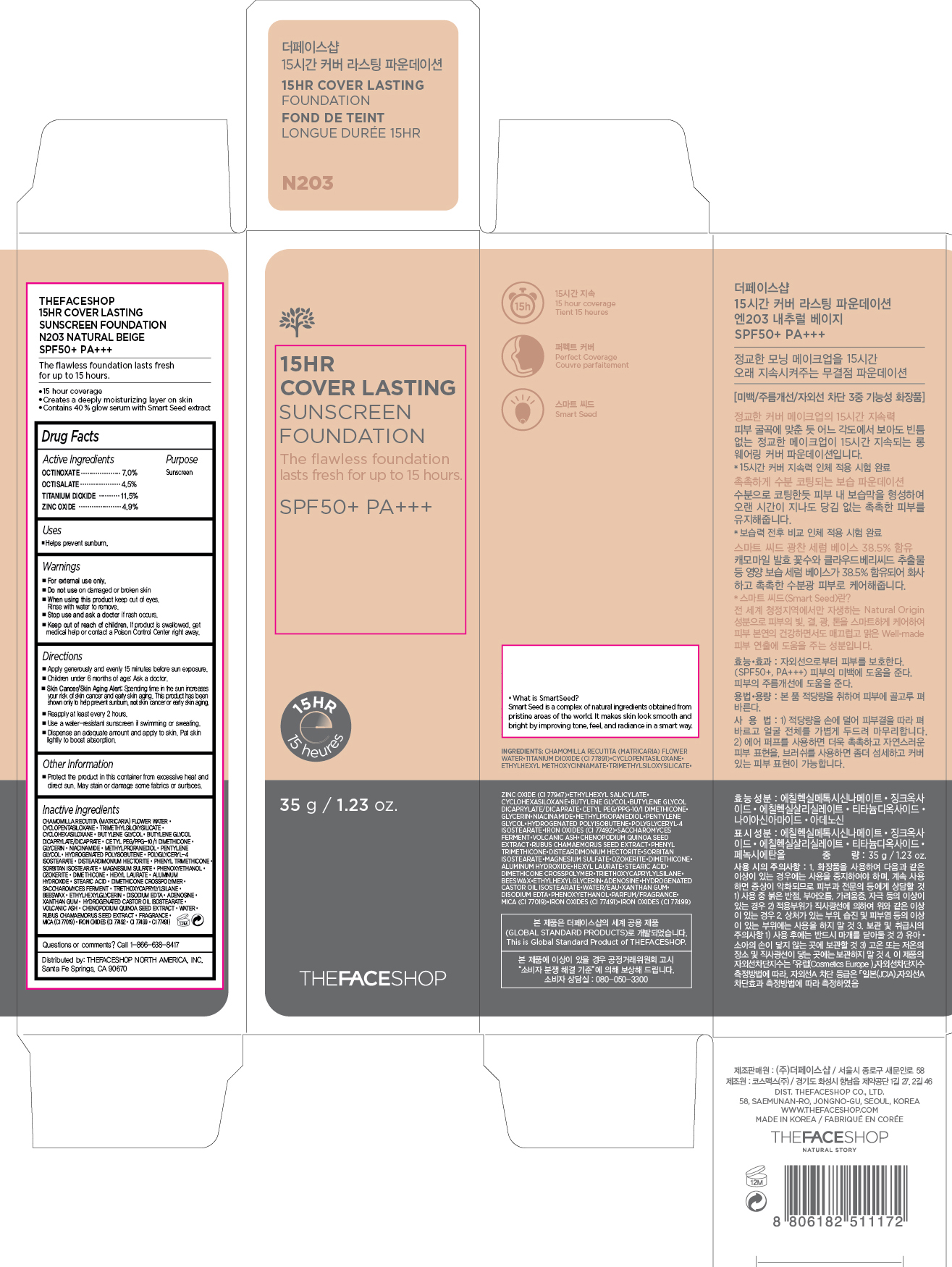 DRUG LABEL: 15HR COVER LASTING
NDC: 51523-371 | Form: CREAM
Manufacturer: THEFACESHOP CO., LTD.
Category: otc | Type: HUMAN OTC DRUG LABEL
Date: 20150921

ACTIVE INGREDIENTS: OCTINOXATE 2.45 g/35 g; OCTISALATE 1.58 g/35 g; TITANIUM DIOXIDE 4.03 g/35 g; ZINC OXIDE 1.72 g/35 g
INACTIVE INGREDIENTS: WATER

15HR COVER LASTING Sunscreen Foundation N203 Natural Beige 34200371

Active Ingredients

Octinoxate 7.0 %

Octisalate 4.5 %

Titanium Dioxide 11.5 %

Zinc Oxide 4.9 %

Purpose

Sunscreen

Sunscreen

Sunscreen

Sunscreen

Uses

Helps prevent sunburn.

Warnings

For external use only.

Do not use on damaged or broken skin

When using this product keep out of eyes. Rinse with water to remove.

Stop use and ask a doctor if rash occurs.

Keep out of reach of children. If product is swallowed, get medical help or contact a Poison Control Center right away.

Directions

Apply generously and evenly 15 minutes before sun exposure.
Children under 6 months of age: Ask a doctor.
Skin Cancer/Skin Aging Alert: Spending time in the sun increases your risk of skin cancer and early skin aging. This product has been shown only to help prevent sunburn, not skin cancer or early skin aging.
Reapply at least every 2 hours.
Use a water-resistant sunscreen if swimming or sweating.

Dispense an adequate amount and apply to skin. Pat skin lightly to boost absorption.

Other Information

Protect the product in this container from excessive heat and direct sun.

May stain or damage some fabrics or surfaces.

Inactive Ingredients

Chamomilla Recutita (Matricaria) Flower Water, Cyclopentasiloxane, Trimethylsiloxysilicate, Cyclohexasiloxane, Butylene Glycol, Butylene Glycol Dicaprylate/Dicaprate, Cetyl PEG/PPG-10/1 Dimethicone, Glycerin, Niacinamide, Methylpropanediol, Pentylene Glycol, Hydrogenated Polyisobutene, Polyglyceryl-4 Isostearate, Disteardimonium Hectorite, Phenyl Trimethicone, Sorbitan Isostearate, Magnesium Sulfate, Phenoxyethanol, Ozokerite, Dimethicone, Hexyl Laurate, Aluminum Hydroxide, Stearic Acid, Dimethicone Crosspolymer, Saccharomyces Ferment, Triethoxycaprylylsilane, Beeswax, Ethylhexylglycerin, Disodium EDTA, Adenosine, Xanthan Gum, Hydrogenated Castor Oil Isostearate, Volcanic Ash, Chenopodium Quinoa Seed Extract, Water, Rubus Chamaemorus Seed Extract, Fragrance, Mica (CI 77019), Iron Oxides (CI 77492, CI 77499, CI 77491)

Questions or comments? Call 1-866-638-8417

Distributed by:

THEFACESHOP NORTH AMERICA, INC.

Santa Fe Springs, CA 90670

PACKAGE LABEL

THEFACESHOP

15HR COVER LASTING SUNSCREEN FOUNDATION

N203 NATURAL BEIGE

SPF50+ PA+++

The flawless foundation lasts fresh for up to 15 hours.

15 hours coverage

Creates a deeply moisturizing layer on skin.

Contains 40% glow serum with Smart Seed extract.